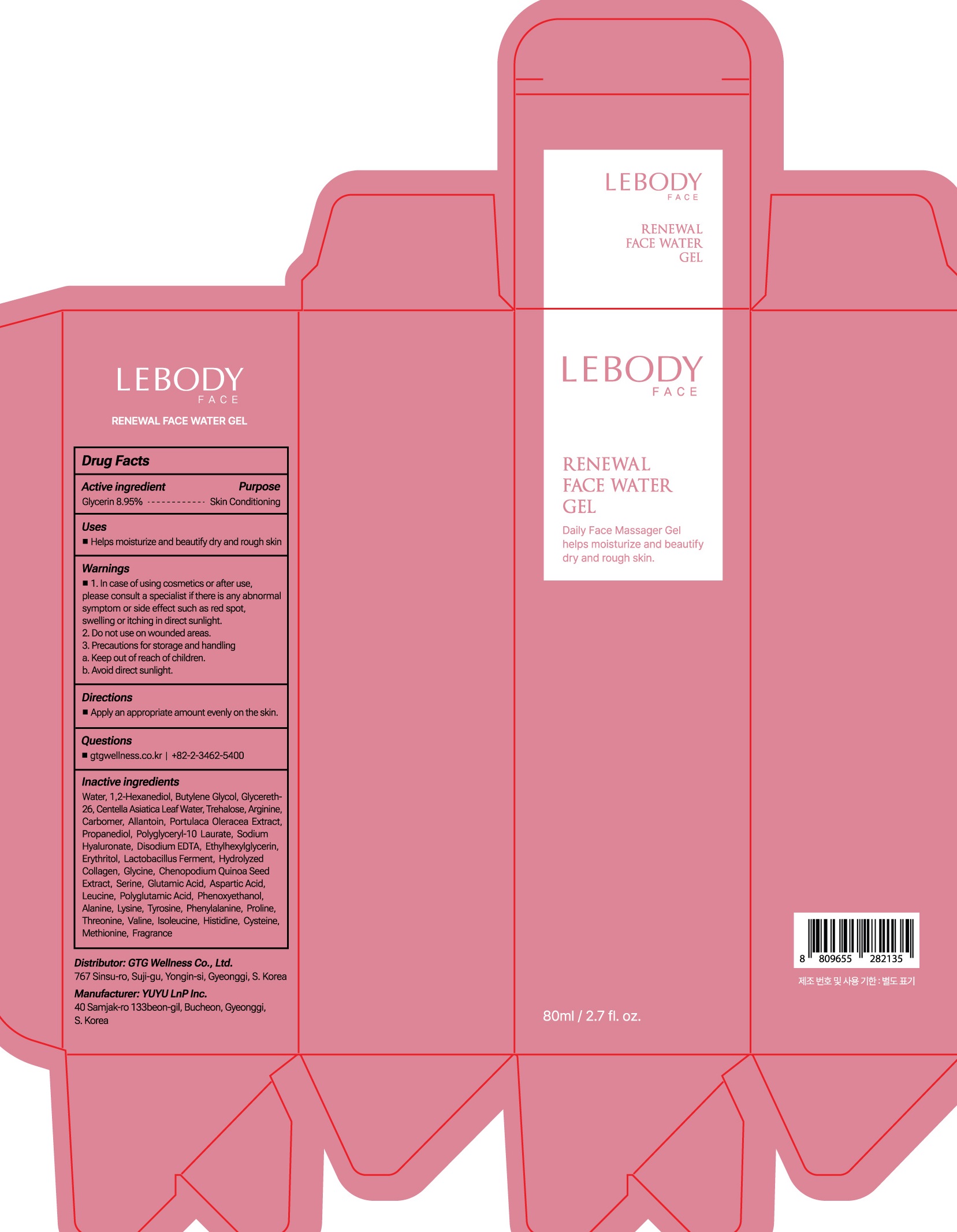 DRUG LABEL: LEBODY FACE RENEWAL FACE WATER
NDC: 71080-0031 | Form: GEL
Manufacturer: GTG WELLNESS CO., LTD.
Category: otc | Type: HUMAN OTC DRUG LABEL
Date: 20230630

ACTIVE INGREDIENTS: Glycerin 8.95 g/100 mL
INACTIVE INGREDIENTS: Water; 1,2-Hexanediol; Butylene Glycol; Glycereth-26

ACTIVE INGREDIENT

Glycerin 8.95%

INACTIVE INGREDIENTS

Water, 1,2-Hexanediol, Butylene Glycol, Glycereth-26, Centella Asiatica Leaf Water, Trehalose, Arginine, Carbomer, Allantoin, Portulaca Oleracea Extract, Propanediol, Polyglyceryl-10 Laurate, Sodium Hyaluronate, Disodium EDTA, Ethylhexylglycerin, Erythritol, Lactobacillus Ferment, Hydrolyzed Collagen, Glycine, Chenopodium Quinoa Seed Extract, Serine, Glutamic Acid, Aspartic Acid, Leucine, Polyglutamic Acid, Phenoxyethanol, Alanine, Lysine, Tyrosine, Phenylalanine, Proline, Threonine, Valine, Isoleucine, Histidine, Cysteine, Methionine, Fragrance

PURPOSE

Skin Conditioning

WARNINGS

1. In case of using cosmetics or after use, please consult a specialist if there is any abnormal symptom or side effect such as red spot, swelling or itching in direct sunlight. 2. Do not use on wounded areas.
3. Precautions for storage and handling a. Keep out of reach of children. b. Avoid direct sunlight.

KEEP OUT OF REACH OF CHILDREN

Uses

■ Helps moisturize and beautify dry and rough skin

Directions

■ Apply an appropriate amount evenly on the skin.

Questions

■ gtgwellness.co.kr | +82-2-3462-5400